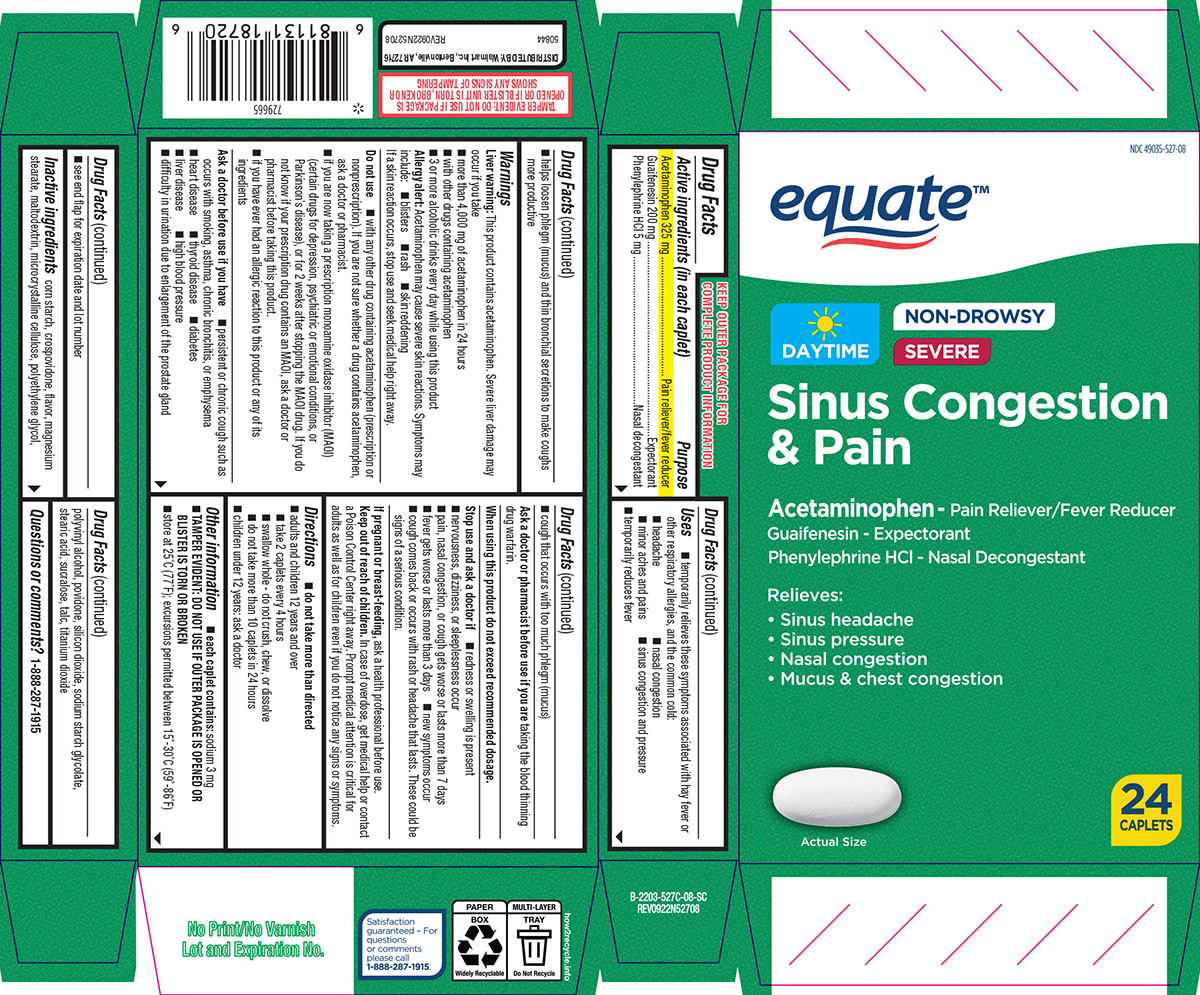 DRUG LABEL: Sinus Congestion and Pain
NDC: 49035-527 | Form: TABLET, FILM COATED
Manufacturer: Wal-Mart Stores Inc
Category: otc | Type: HUMAN OTC DRUG LABEL
Date: 20251231

ACTIVE INGREDIENTS: ACETAMINOPHEN 325 mg/1 1; GUAIFENESIN 200 mg/1 1; PHENYLEPHRINE HYDROCHLORIDE 5 mg/1 1
INACTIVE INGREDIENTS: STARCH, CORN; CROSPOVIDONE, UNSPECIFIED; MAGNESIUM STEARATE; MALTODEXTRIN; MICROCRYSTALLINE CELLULOSE; POLYETHYLENE GLYCOL, UNSPECIFIED; POLYVINYL ALCOHOL, UNSPECIFIED; POVIDONE, UNSPECIFIED; SILICON DIOXIDE; SODIUM STARCH GLYCOLATE TYPE A POTATO; STEARIC ACID; SUCRALOSE; TALC; TITANIUM DIOXIDE

Equate 44-527C

Active ingredients (in each caplet)

Acetaminophen 325 mg
Guaifenesin 200 mg
Phenylephrine HCl 5 mg

Purpose

Pain reliever/fever reducer
Expectorant
Nasal decongestant

Uses

- temporarily relieves these symptoms associated with hay fever or other respiratory allergies, and the common cold:
  - headache
  - minor aches and pains
  - nasal congestion
  - sinus congestion and pressure
- helps loosen phlegm (mucus) and thin bronchial secretions to make coughs more productive
- temporarily reduces fever

Warnings

Liver warning: This product contains acetaminophen. Severe liver damage may occur if you take:

- more than 4,000 mg of acetaminophen in 24 hours
- with other drugs containing acetaminophen
- 3 or more alcoholic drinks every day while using this product

Allergy alert: Acetaminophen may cause severe skin reactions. Symptoms may include:

- blisters
- rash
- skin reddening

If a skin reaction occurs, stop use and seek medical help right away.

Do not use

- with any other drug containing acetaminophen (prescription or nonprescription). If you are not sure whether a drug contains acetaminophen, ask a doctor or pharmacist.
- if you are now taking a prescription monoamine oxidase inhibitor (MAOI) (certain drugs for depression, psychiatric or emotional conditions, or Parkinson's disease), or for 2 weeks after stopping the MAOI drug. If you do not know if your prescription drug contains an MAOI, ask a doctor or pharmacist before taking this product.
- if you have ever had an allergic reaction to this product or any of its ingredients

Ask a doctor before use if you have

- diabetes
- heart disease
- thyroid disease
- liver disease
- high blood pressure
- cough that occurs with too much phlegm (mucus)
- persistent or chronic cough such as occurs with smoking, asthma, chronic bronchitis, or emphysema
- difficulty in urination due to enlargement of the prostate gland

Ask a doctor or pharmacist before use if you are

taking the blood thinning drug warfarin.

When using this product

do not exceed recommended dosage.

Stop use and ask a doctor if

- nervousness, dizziness, or sleeplessness occur
- pain, nasal congestion, or cough gets worse or lasts more than 7 days
- new symptoms occur
- fever gets worse or lasts more than 3 days
- redness or swelling is present
- cough comes back or occurs with rash or headache that lasts. These could be signs of a serious condition.

If pregnant or breast-feeding,

ask a health professional before use.

Keep out of reach of children.

In case of overdose, get medical help or contact a Poison Control Center right away. Prompt medical attention is critical for adults as well as for children even if you do not notice any signs or symptoms.

Directions

- do not take more than directed
- adults and children 12 years and over
  - take 2 caplets every 4 hours
  - swallow whole - do not crush, chew, or dissolve
  - do not take more than 10 caplets in 24 hours
- children under 12 years: ask a doctor

Other information

- each caplet contains: sodium 3 mg
- TAMPER EVIDENT: DO NOT USE IF OUTER PACKAGE IS OPENED OR BLISTER IS TORN OR BROKEN
- store at 25ºC (77ºF); excursions permitted between 15º-30ºC (59º-86ºF)
- see end flap for expiration date and lot number

Inactive ingredients

corn starch, crospovidone, flavor, magnesium stearate, maltodextrin, microcrystalline cellulose, polyethylene glycol, polyvinyl alcohol, povidone, silicon dioxide, sodium starch glycolate, stearic acid, sucralose, talc, titanium dioxide

Questions or comments?

1-888-287-1915

Principal Display Panel

NDC 49035-527-08

equate™

Daytime Non-Drowsy
Severe

Sinus Congestion
& Pain

Acetaminophen- Pain Reliever/Fever Reducer
Guaifenesin- Expectorant
Phenylephrine HCl- Nasal Decongestant

Relieves:
• Sinus headache
• Sinus pressure
• Nasal congestion
• Mucus & chest congestion

24
CAPLETS

Actual Size

TAMPER EVIDENT: DO NOT USE IF PACKAGE IS
OPENED OR IF BLISTER UNIT IS TORN, BROKEN OR
SHOWS ANY SIGNS OF TAMPERING

Satisfaction
guaranteed - For
questions
or comments
please call
1-888-287-1915.

DISTRIBUTED BY: Walmart Inc., Bentonville, AR 72716
50844 REV0922N52708

Equate 44-527C